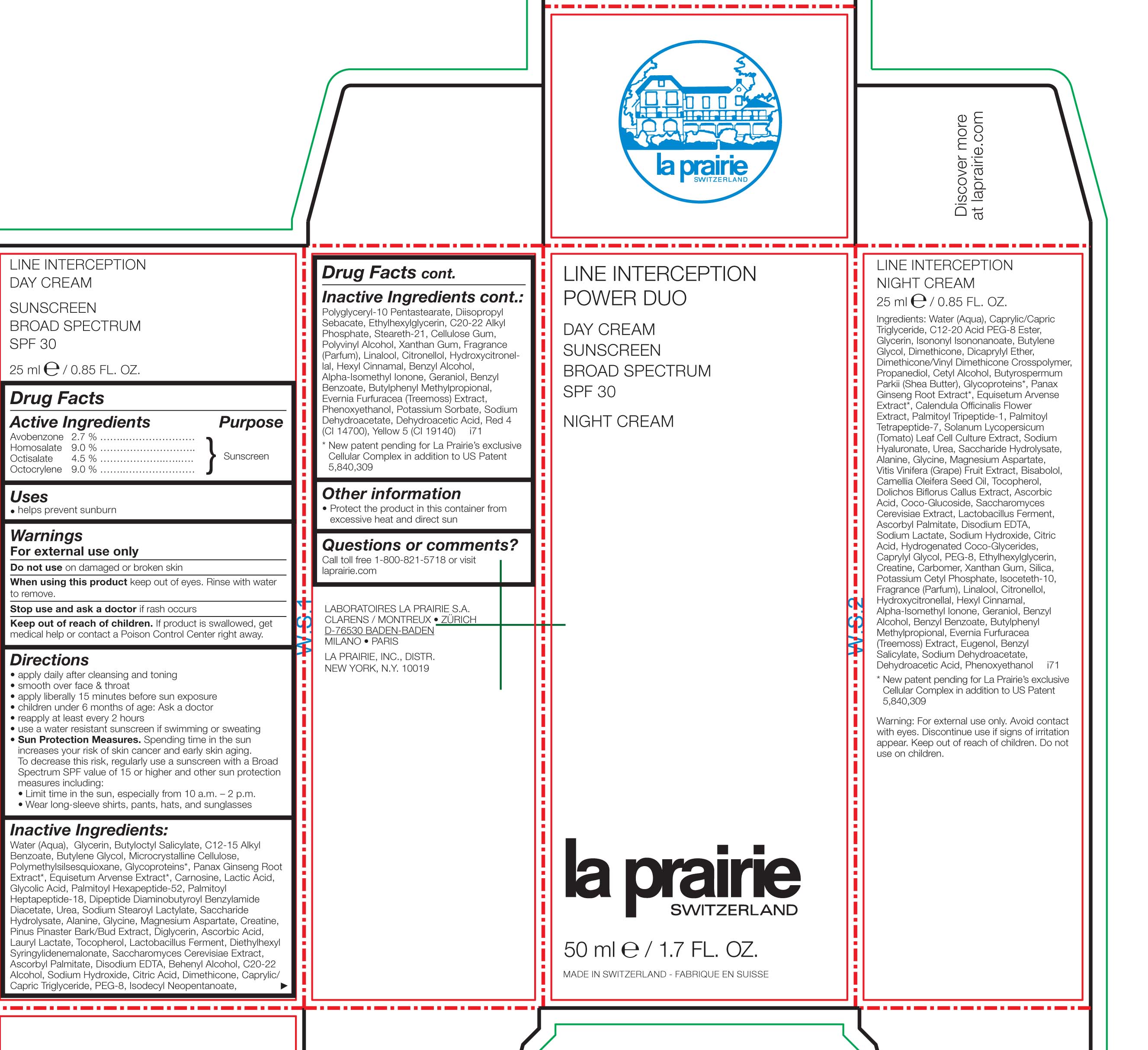 DRUG LABEL: Line Interception Power Duo Day Cream Suncreen
NDC: 68807-326 | Form: CREAM
Manufacturer: Temmentec AG
Category: otc | Type: HUMAN OTC DRUG LABEL
Date: 20170105

ACTIVE INGREDIENTS: AVOBENZONE 2.7 g/100 kg; HOMOSALATE 9.0 g/100 kg; OCTISALATE 4.5 g/100 kg; OCTOCRYLENE 9.0 g/100 kg
INACTIVE INGREDIENTS: WATER; GLYCERIN; BUTYLOCTYL SALICYLATE; ALKYL (C12-15) BENZOATE; BUTYLENE GLYCOL; CELLULOSE, MICROCRYSTALLINE; POLYMETHYLSILSESQUIOXANE (4.5 MICRONS); GLYCOPROTEIN HORMONES ALPHA CHAIN; ASIAN GINSENG; EQUISETUM ARVENSE BRANCH; CARNOSINE; LACTIC ACID; GLYCOLIC ACID; DIPEPTIDE DIAMINOBUTYROYL BENZYLAMIDE DIACETATE; UREA; SODIUM STEAROYL LACTYLATE; INVERT SUGAR; ALANINE; GLYCINE; MAGNESIUM ASPARTATE; CREATINE; DIGLYCERIN; ASCORBIC ACID; LAURYL LACTATE; TOCOPHEROL; LACTOBACILLUS REUTERI; DIETHYLHEXYL SYRINGYLIDENEMALONATE; SACCHAROMYCES CEREVISIAE; ASCORBYL PALMITATE; EDETATE DISODIUM; DOCOSANOL; SODIUM HYDROXIDE; CITRIC ACID MONOHYDRATE; DIMETHICONE; POLYETHYLENE GLYCOL 400; ISODECYL NEOPENTANOATE; DIISOPROPYL SEBACATE; ETHYLHEXYLGLYCERIN; C20-22 ALKYL PHOSPHATE; STEARETH-21; CARBOXYMETHYLCELLULOSE SODIUM, UNSPECIFIED FORM; POLYVINYL ALCOHOL; XANTHAN GUM; LINALOOL, (+/-)-; .BETA.-CITRONELLOL, (R)-; HYDROXYCITRONELLAL; .ALPHA.-HEXYLCINNAMALDEHYDE; BENZYL ALCOHOL; ISOMETHYL-.ALPHA.-IONONE; GERANIOL; BENZYL BENZOATE; BUTYLPHENYL METHYLPROPIONAL; PSEUDEVERNIA FURFURACEA; PHENOXYETHANOL; POTASSIUM SORBATE; SODIUM DEHYDROACETATE; DEHYDROACETIC ACID; FD&C RED NO. 4; FD&C YELLOW NO. 5

Line Interception Power Duo Day Cream Sunscreen Broad Spectrum SPF 30

Active Ingredients Purpose

Avobenzone 2.7% .............

Homosalate 9.0% ............. Sunscreen

Octisalate 4.5% ............

Octocrylene 9.0% ...........

PURPOSE

Helps prevent sunburn

Keep out of reach of children. If product is swallowed, get medical help or contact a Poison Control Center right away.

Stop use and ask a doctor if rash occurs

WARNINGS

For external use only

Do not use on damaged or broken skin

When using this product keep out of eyes. Rinse with water to remove

Directions

- apply daily after cleansing and toning
- smooth over face & throat
- apply liberally 15 minutes before sun exposure
- children und 6 months of age: Ask a doctor
- reapply at least every 2 hours
- use a water resistan sunscreen if swimming or sweating
- Sun Protection Measures. Spending time in the sunincreases your risk of skin cancer and early skin aging. To decrease this risk, regularly use a sunscreen with a Broad Spectrum SPF value of 15 or higher and oher sun protection measures including:
- Limit time in the sun, especially from 10 a.m. - 2 p.m.
- Wear long-sleeve shirts, pants, hats, and sunglasses

Inactive Ingredients:

Water (Aqua), Glycerin, Butyloctyl Salicylate, C12-15 Alkyl Benzoate, Butylene Glycol, Microcrystalline Cellulose, Polymethylsilsquioxane, Glycoproteins, Panax Ginseng Root Extract, Equisetum Arvense Extract, Carnosine, Lactic Acid, Glycolic Acid, Palmitoyl Hexapeptide-52, Palmitoyl Heptapeptide-18, Dipeptide Diaminobutyroyl Benzylamide Diacetate, Urea, Sodium Stearoyl Lactylate, Saccharide Hydrolysate, Alanine, Glycine, Magnesium Aspartate, Creatine, Pinus Pinaster Bark/Bud Extract, Diglycerin, Ascorbic Acid, Lauryl Lactate, Tocopherol, Lactobaillus Ferment, Diethylhexyl Syringylidenemalonate, Saccharomyces Cerevisiae Extract, Ascorbyl Palmitate, Disodium EDTA, Behenyl Alcohol, C20-22 Alcohol, Sodium Hydroxide, Citric Acid, Dimethicone, Caprylic/Capric Triglyceride, PEG-8, Isodecyl Neopentanoate, Polyglyceryl-10 Pentastearate, Diisopropyl Sebacate, Ethylhexylglycerin, C20-22 Alkyl Phosphate, Steareth-21, Cellulose Gum, Polyvinyl Alcohol, Xanthan Gum, Fragrance (Parfum) Linalool, Citronellol, Hydroxycitronellal, Hexyl Cinnamal, Benzyl Benzoate, Butylphenyl Methylpropional, Evernia Furfuracea (Treemoss) Extract, Phenoxyethanol, Potassium Sorbate, Sodium Dehydroacetate, Dehydroacetic Acid, Reg 4 (CI 14700), Yellow 5 (CI 19140)

PACKAGE LABEL

La Prairie

Line Interception Anti-Wrinkle Day - Night Intervention

Day Cream

Sunscreen

Broad Spectrum

SPF30

50 ml e / 1.7 FL. OZ.